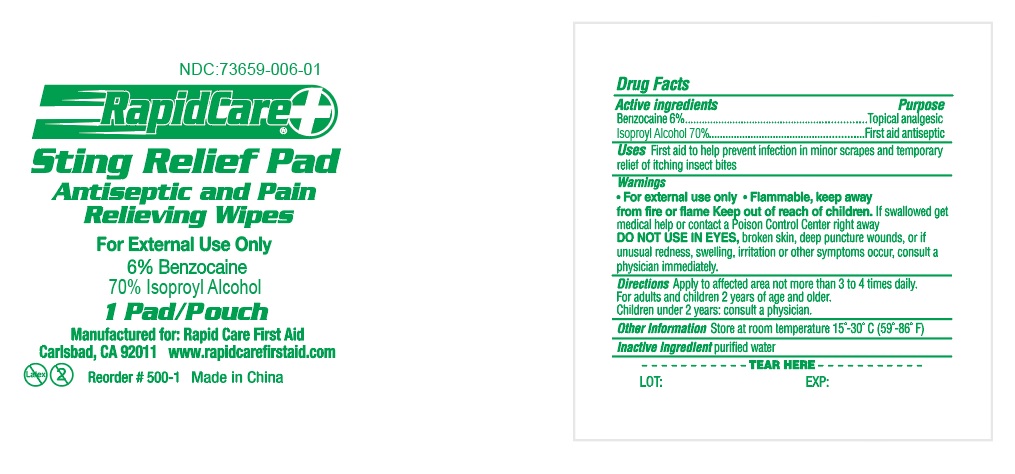 DRUG LABEL: Sting Relief
NDC: 73659-009 | Form: SWAB
Manufacturer: Rapid Care, Inc
Category: otc | Type: HUMAN OTC DRUG LABEL
Date: 20211014

ACTIVE INGREDIENTS: ISOPROPYL ALCOHOL 0.7 mL/1 1; BENZOCAINE 0.06 g/1 1
INACTIVE INGREDIENTS: WATER

RapidCare - Sting Relief - 1pc

Active Ingredients

Benocaine 6%

Isoproyl Alcohol 70%

Purpose

Topical analgesic

Antiseptic

Use

First aid to help prevent infection in minor scrapes and temporary relief of itching insect bites

Warnings

For external use only.

WARNINGS AND PRECAUTIONS

Flammable, keep away from fire or flame.

DO NOT USE IN EYES

, broken skin, deep punture wounds, or if unusual redness, swelling, irritation or other symptoms occur, consult a physician immediately.

Stop use

if irritation and redness develop. If condition continues, consult your heath care practitioner.

Keep out of reach of children.

If swallowed get medical help or contact a Poison Control right away.

Directions

Apply to affect area not more than 3 to 4 times daily. For adults and children 2 years of age and older. Children under 2 years: consult a physician.

Other Information

store at room temperature 15° - 30° C (59° - 86° F)

Inactive ingredient

purified water